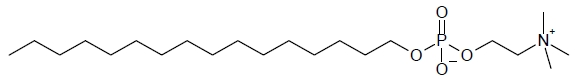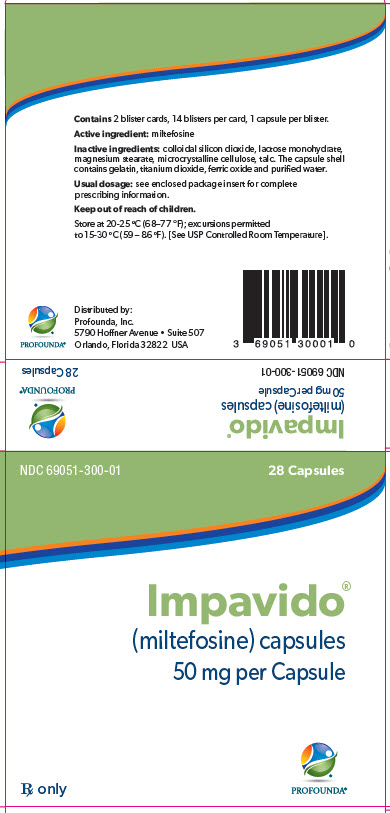 DRUG LABEL: IMPAVIDO
NDC: 69051-300 | Form: CAPSULE
Manufacturer: Profounda, Inc.
Category: prescription | Type: HUMAN PRESCRIPTION DRUG LABEL
Date: 20251218

ACTIVE INGREDIENTS: MILTEFOSINE 50 mg/1 1
INACTIVE INGREDIENTS: SILICON DIOXIDE; CELLULOSE, MICROCRYSTALLINE; LACTOSE MONOHYDRATE; TALC; MAGNESIUM STEARATE; GELATIN; TITANIUM DIOXIDE; FERRIC OXIDE RED; WATER

HIGHLIGHTS OF PRESCRIBING INFORMATION

These highlights do not include all the information needed to use IMPAVIDO safely and effectively. See full prescribing information for IMPAVIDO.
IMPAVIDO (miltefosine) capsules, for oral use
Initial U.S. Approval: 2014

WARNING: EMBRYO-FETAL TOXICITY

See full prescribing information for complete boxed warning.

IMPAVIDO may cause fetal harm. Fetal death and teratogenicity, occurred in animals administered miltefosine at doses lower than the recommended human dose. Do not administer IMPAVIDO to pregnant women. Obtain a serum or urine pregnancy test in females of reproductive potential prior to prescribing IMPAVIDO.

Advise females of reproductive potential to use effective contraception during therapy and for 5 months after therapy (4.1, 5.1, 8.1, 8.8, 13.1).

1 INDICATIONS AND USAGE

IMPAVIDO is an antileishmanial drug indicated in adults and adolescents ≥12 years of age weighing ≥30 kg (66 lbs) for treatment of:

- Visceral leishmaniasis due to Leishmania donovani (1).
- Cutaneous leishmaniasis due to Leishmania braziliensis, Leishmania guyanensis, and Leishmania panamensis (1).
- Mucosal leishmaniasis due to Leishmania braziliensis (1).

Limitations of use: Leishmania species evaluated in clinical trials were based on epidemiologic data. There may be geographic variation in the response of the same Leishmania species to IMPAVIDO (1, 14). The efficacy of IMPAVIDO in the treatment of other Leishmania species has not been evaluated.

2 DOSAGE AND ADMINISTRATION

Administer with food to ameliorate gastrointestinal adverse reactions.

- 30 to 44 kg: one 50 mg capsule twice daily for 28 consecutive days (2).
- 45 kg or greater: one 50 mg capsule three times daily for 28 consecutive days (2).

3 DOSAGE FORMS AND STRENGTHS

Each IMPAVIDO capsule for oral use contains 50 mg miltefosine (3).

4 CONTRAINDICATIONS

- Pregnancy (4.1, 8.1, 8.8, 13.1).
- Sjögren-Larsson-Syndrome (4.2, 12.3).
- Hypersensitivity to miltefosine or any of its excipients (4.3).

5 WARNINGS AND PRECAUTIONS

- Embryo-Fetal Toxicity. Do not use in pregnant women. Obtain a urine or serum pregnancy test prior to initiation of therapy. Advise use of effective contraception in females of reproductive potential (Boxed Warning, 5.1, 8.1, 8.8, 13.1).
- Reproductive effects. Miltefosine caused testicular atrophy and impaired fertility in male rats and impaired fertility in female rats. Advise patients of reproductive toxicities in animal studies and that the potential effects on human fertility have not been adequately evaluated (13.1).
- Renal Effects. Monitor serum creatinine during therapy and for 4 weeks after end of therapy (5.3, 6.1).
- Hepatic Effects. Monitor transaminases and bilirubin during therapy (5.4, 6.1).
- Gastrointestinal Effects. Encourage fluid intake (5.5).
- Thrombocytopenia. Monitor platelet count during therapy for visceral leishmaniasis (5.6, 6.1).
- Absorption of Oral Contraceptives. Advise use of alternative method of contraception if vomiting and/or diarrhea occur (5.7).
- Stevens-Johnson syndrome. Discontinue IMPAVIDO (5.8).

6 ADVERSE REACTIONS

- Adverse reactions occurring in ≥2% of patients include nausea, vomiting, diarrhea, headache, decreased appetite, dizziness, abdominal pain, pruritus, somnolence, elevated transaminases, and elevated creatinine (6.1).

To report SUSPECTED ADVERSE REACTIONS, contact Profounda, Inc. at 1-866-588-5405 or FDA at 1-800-FDA-1088 or www.fda.gov/medwatch.

7 DRUG INTERACTIONS

- IMPAVIDO did not inhibit human cytochrome P450 enzymes in vitro.
- IMPAVIDO did not induce cytochrome 3A activity in rats(7, 12.3).

8 USE IN SPECIFIC POPULATIONS

- Pregnancy: IMPAVIDO should not be used during pregnancy. Obtain a urine or serum pregnancy test in females of reproductive potential prior to prescribing (4.1, 5.1, 8.1, 8.8, 13.1).
- Nursing Mothers: Discontinue drug or nursing depending on importance of drug to mother. Avoid breastfeeding for 5 months after IMPAVIDO therapy (8.3).
- Females and Males of Reproductive Potential: Advise females to use effective contraception during therapy and for 5 months after therapy. Advise patients of reproductive toxicities in animals, and that the potential for impaired fertility in humans has not been adequately evaluated (5.1, 5.2, 8.8).

FULL PRESCRIBING INFORMATION

WARNING: EMBRYO-FETAL TOXICITY

IMPAVIDO may cause fetal harm. Fetal death and teratogenicity occurred in animals administered miltefosine at doses lower than the recommended human dose. Do not administer IMPAVIDO to pregnant women. Obtain a serum or urine pregnancy test in females of reproductive potential prior to prescribing IMPAVIDO. Females of reproductive potential should be advised to use effective contraception during IMPAVIDO therapy and for 5 months after therapy [see Contraindications (4.1), Warnings and Precautions (5.1), Use in Specific Populations (8.1, 8.8) and Nonclinical Toxicology (13.1)] .

1 INDICATIONS AND USAGE

IMPAVIDO (miltefosine) capsules are indicated in adults and adolescents ≥12 years of age weighing ≥ 30 kg for the treatment of:

- Visceral leishmaniasis caused by Leishmania donovani [see Clinical Trials (14.1)] .
- Cutaneous leishmaniasis caused by Leishmania braziliensis, Leishmania guyanensis, and Leishmania panamensis [see Clinical Trials (14.2)] .
- Mucosal leishmaniasis caused by Leishmania braziliensis [see Clinical Trials (14.3)] .

Limitations of Use:

- Leishmania species studied in clinical trials evaluating IMPAVIDO were based on epidemiologic data [see Clinical Trials (14.1, 14.2)] .
- There may be geographic variation in clinical response of the same Leishmania species to IMPAVIDO [see Clinical Trials (14.1, 14.2)] .
- The efficacy of IMPAVIDO in the treatment of other Leishmania species has not been evaluated.

2 DOSAGE AND ADMINISTRATION

The treatment duration is 28 consecutive days. Administer with food to ameliorate gastrointestinal adverse reactions.

Table 1: Miltefosine Dosage
Weight | Dosage and Administration
30 kg to 44 kg | One 50 mg capsule twice daily with food (breakfast and dinner)
45 kg or greater | One 50 mg capsule three times daily with food (breakfast, lunch, and dinner)

3 DOSAGE FORMS AND STRENGTHS

IMPAVIDO® (miltefosine) oral capsules are opaque, red, hard gelatin capsules with “PLB” imprinted on the capsule body and “MILT 50” imprinted on the cap using a white ink. Each capsule contains 50 mg miltefosine [see Description (11), How Supplied/Storage and Handling (16)] .

4 CONTRAINDICATIONS

4.1 Pregnancy

IMPAVIDO may cause fetal harm. IMPAVIDO is contraindicated in pregnant women. Obtain a urine or serum pregnancy test prior to prescribing IMPAVIDO [see Boxed Warning and Use in Specific Populations (8.1)] .

4.2 Sjögren-Larsson-Syndrome

IMPAVIDO is contraindicated in patients who have Sjögren-Larsson-Syndrome [see Clinical Pharmacology (12.3)] .

4.3 Hypersensitivity

IMPAVIDO is contraindicated in patients who are hypersensitive to miltefosine or any IMPAVIDO excipients.

5 WARNINGS AND PRECAUTIONS

5.1 Embryo-Fetal Toxicity

Miltefosine may cause fetal harm. Embryo-fetal toxicity, including death and teratogenicity, was observed in animals administered miltefosine prior to mating, during early pregnancy, and during organogenesis at doses lower than the maximum recommended human dose (MRHD). Do not use IMPAVIDO in pregnant women. Obtain a urine or serum pregnancy test prior to prescribing IMPAVIDO to females of reproductive potential. Advise females of reproductive potential to use effective contraception during IMPAVIDO therapy and for 5 months after completion of therapy [see Boxed Warning, Contraindications (4.1) and Use in Specific Populations (8.1, 8.8)] .

5.2 Reproductive Effects

Females

Miltefosine caused impaired fertility in rats and reversible follicular atresia and diestrus in dogs at doses approximately 1.0 and 0.2 times respectively the MRHD based on body surface area comparisons [see Nonclinical Toxicology (13.1)] . Effects on human female fertility have not been formally studied.

Males

Miltefosine caused reduced viable sperm counts and impaired fertility in rats at doses approximately 0.4 times the MRHD [see Nonclinical Toxicology (13.1) ]. A higher dose in rats, approximately 1.0 times the MRHD, caused testicular atrophy and impaired fertility that did not fully reverse 10 weeks after drug administration ended.

Scrotal pain and decreased or absent ejaculation during therapy have been reported during IMPAVIDO therapy [see Adverse Reactions (6.2) ]. The effects of IMPAVIDO on human male fertility have not been adequately studied.

Advise women and men of the animal fertility findings, and that the potential for impaired fertility with IMPAVIDO therapy in humans has not been adequately evaluated.

5.3 Renal Effects

Elevations of serum creatinine (Cr) were noted in clinical trials evaluating IMPAVIDO in the treatment of cutaneous, mucosal and visceral leishmaniasis. Monitor renal function weekly in patients receiving IMPAVIDO during therapy and for 4 weeks after end of therapy [see Adverse Reactions (6.1)] .

5.4 Hepatic Effects

Elevations in liver transaminases (ALT, AST) and bilirubin were noted in clinical trials evaluating IMPAVIDO in the treatment of visceral leishmaniasis. Monitor liver transaminases (ALT, AST) and bilirubin during therapy in patients receiving IMPAVIDO [see Adverse Reactions (6.1)] .

5.5 Gastrointestinal Effects

Vomiting and/or diarrhea commonly occur during IMPAVIDO administration and may result in volume depletion. Encourage fluid intake to avoid volume depletion [see Adverse Reactions (6.1)] .

5.6 Thrombocytopenia

Thrombocytopenia during therapy has been reported in patients treated for visceral leishmaniasis. Monitor platelet count during therapy for visceral leishmaniasis [see Adverse Reactions (6.1, 6.2)] .

5.7 Absorption of Oral Contraceptives

Vomiting and/or diarrhea occurring during IMPAVIDO therapy may affect the absorption of oral contraceptives, and therefore compromise their efficacy. If vomiting and/or diarrhea occur during IMPAVIDO therapy, advise females to use additional non-hormonal or alternative method(s) of effective contraception.

5.8 Stevens-Johnson Syndrome

Stevens-Johnson syndrome has been reported during IMPAVIDO therapy. Discontinue IMPAVIDO if an exfoliative or bullous rash is noted during therapy [see Adverse Reactions (6.1)] .

6 ADVERSE REACTIONS

Because clinical trials are conducted under widely varying conditions, adverse reaction rates observed in the clinical trials of a drug cannot be directly compared to rates in the clinical trials of another drug and may not reflect the rates observed in practice.

6.1 Clinical Trials Experience

Visceral Leishmaniasis

One Phase 3 trial was conducted in patients ≥ 12 years of age in India. Two-hundred and ninety-nine (299) patients (211 men and 88 women) received oral IMPAVIDO at a target dose of 2.5 mg/kg/day for 28 days (50 mg capsule once daily if weight was less than 25 kg and 50 mg capsule twice daily if weight was 25 kg or greater). Patients ranged between 12 and 64 years of age. Weight ranged between 15 and 67 kg (mean weight 38.6 kg) and BMI ranged between 8.2 and 24 (mean 16.1). Ninety-nine (99) patients received 1 mg/kg/day amphotericin B deoxycholate intravenously every other day for 15 doses. A statistically significant higher percentage of men received IMPAVIDO compared to amphotericin B.

Less than 1% of patients who received IMPAVIDO died (2/299) and no patient who received amphotericin B died. Serious adverse reactions were reported in 2% of IMPAVIDO recipients (6/299) and 1% of amphotericin B recipients (1/99). Approximately 3% of patients discontinued treatment in each treatment arm due to an adverse reaction. Serious adverse reactions and adverse reactions leading to drug discontinuation that were thought to be related or possibly related to IMPAVIDO included Stevens-Johnson syndrome, melena and thrombocytopenia, arthritis and skin rash, CTCAE [Common Terminology Criteria for Adverse Events] Grade 4 diarrhea (≥10 stools per day) and CTCAE Grade 4 hyperbilirubinemia (≥10x upper limit of normal ULN).

Table 2: Treatment Emergent Adverse Reactions Occurring in ≥2% of Visceral Leishmaniasis Patients Receiving IMPAVIDO
System Organ Class Preferred Term | IMPAVIDO N = 299 | Amphotericin B Deoxycholate N = 99
Gastrointestinal Disorders
Diarrhea | 61 (20.4%) | 6 (6.1%)
Vomiting | 113 (37.8%) | 20 (20.0%)
General Disorders
Asthenia | 19 (6.3%) | 4 (4.0%)
Metabolism and Nutrition Disorders
Decreased Appetite | 69 (23.1%) | 22 (22.2%)

In this study, creatinine (Cr) elevations ≥ 1.5 times above baseline occurred in approximately 10% of IMPAVIDO recipients and in 40% of amphotericin B recipients at the end of therapy. Ten percent of subjects in each arm had Cr elevations ≥1.5 times above baseline at 6 months follow up. No IMPAVIDO recipient discontinued therapy due to Cr elevation.

Elevations of transaminases during therapy occurred in up to half of IMPAVIDO recipients and up to a third of amphotericin B recipients. The elevations were mild (< 3x ULN) or moderate (3-5x ULN) in 94% and 6% respectively of IMPAVIDO-treated patients who experienced an elevation. No patient discontinued therapy due to elevations in transaminases.

At the end of therapy, 62% and 2.4% of IMPAVIDO recipients and 54% and 2% of amphotericin B recipients had platelet count < 150,000 and < 50,000 respectively.

Cutaneous Leishmaniasis

The efficacy of IMPAVIDO in the treatment of cutaneous leishmaniasis was evaluated in one placebo-controlled trial conducted in Colombia and Guatemala and in two comparative trials conducted in Bolivia and Brazil respectively. In the placebo-controlled trial, eighty-nine (89) patients ≥12 years of age received a target IMPAVIDO dose of 2.5 mg/kg/day for 28 days and forty-four (44) received placebo. In the comparative trials, one hundred and twenty (120) patients ≥12 years of age received a target IMPAVIDO dose of 2.5 mg/kg/day for 28 days and fifty eight (58) patients received 20 mg/kg/day pentavalent antimony (meglumine) parenterally for 20 days.

Table 3: Adverse Reactions Occurring in ≥2% of IMPAVIDO-Treated Patients ≥12 Years of Age with Cutaneous Leishmaniasis in the Placebo-Controlled Trial
System Organ Class Preferred Term | IMPAVIDO N = 89 | Placebo N = 44
Ear and Labyrinth Disorders
Motion Sickness | 26 (29.2%) | 10 (22.7%)
Gastrointestinal Disorders
Abdominal Pain | 10 (11.2%) | 3 (6.8%)
Diarrhea | 7 (7.9%) | 2 (4.5%)
Nausea | 32 (35.9%) | 5 (11.1%)
Vomiting | 4 (4.5%) | 0
General and Administration Site Disorders
Malaise | 3 (3.4%) | 1 (2.3%)
Pyrexia | 5 (5.6%) | 2 (4.5%)
Nervous System Disorders
Dizziness | 4 (4.5%) | 0
Headache | 25 (28.1%) | 10 (22.7%)
Somnolence | 3 (3.4%) | 0
Skin and Subcutaneous Tissue Disorders
Pruritus | 4 (4.5%) | 0

Table 4: Adverse Reactions Occurring in ≥2% of IMPAVIDO-Treated Patients ≥ 12 Years of Age with Cutaneous Leishmaniasis in Two Comparative Trials
System Organ Class Preferred Term | IMPAVIDO N = 120 | Meglumine N = 58
Gastrointestinal Disorders
Abdominal Pain | 9 (7.5%) | 3 (5.2%)
Diarrhea | 18 (15.0%) | 3 (5.2%)
Nausea | 50 (41.7%) | 3 (5.2%)
Vomiting | 33 (27.5%) | 0
Infections and Infestations
Lymphangitis | 7 (5.8%) | 0
Metabolism and Nutrition Disorders
Decreased Appetite | 13 (10.8%) | 4 (5.8%)
Nervous System Disorders
Dizziness | 15 (12.5%) | 4 (6.9%)
Skin and Subcutaneous Tissue Disorders
Pruritus | 7 (5.8%) | 0

In the placebo controlled trial, 12/89 (13.4%) IMPAVIDO subjects had Cr increases of 1.5-3 times above baseline, compared to 2/44 (4.5%) placebo subjects at end of therapy. In the comparative trial, a similar percentage of subjects who received IMPAVIDO or pentavalent antimony had Cr elevations above baseline at 3 and 6 months after therapy (approximately 5%). Approximately 25% of IMPAVIDO subjects and 11% of pentavalent antimony subjects had Cr elevations 1.5-3 times above baseline at the end of therapy in the two active controlled trials. The frequency of AST and ALT increase above upper limit of normal at end of therapy was similar in IMPAVIDO and placebo recipients (approximately 5%).

Other adverse events seen at <2% incidence in the IMPAVIDO group included anemia, lymphadenopathy, abdominal distension, constipation, dysphagia, flatulence, fatigue, malaise, abscess, cellulitis, ecthyma, paresthesia, testicular pain, testicular swelling, Stevens-Johnson syndrome, urticaria, rash, pyoderma.

6.2 Postmarketing Experience

The following adverse reactions have been identified during use of IMPAVIDO worldwide. Because these reactions are reported voluntarily from a population of uncertain size, it is not always possible to reliably estimate their frequency or establish a causal relationship to drug exposure.

Blood and Lymphatics Disorders: thrombocytopenia, agranulocytosis

Gastrointestinal Disorders: melena

General Disorders: generalized edema, peripheral edema

Hepatobiliary Disorders: jaundice

Nervous System Disorders: seizure

Reproductive System and Breast Disorders: scrotal pain, decreased ejaculate volume, absent ejaculation.

Vascular Disorders: epistaxis

7 DRUG INTERACTIONS

In vitro and animal metabolism studies showed that miltefosine did not markedly induce or inhibit the activity of the major human cytochrome P450 enzymes [see Clinical Pharmacology (12.3)] . The potential of miltefosine to interact with drug transporters has not been evaluated.

8 USE IN SPECIFIC POPULATIONS

8.1 Pregnancy

Pregnancy Category D

Risk Summary

IMPAVIDO may cause fetal harm. Human pregnancy data are not available, however, embryo-fetal toxicity including death and teratogenicity, was observed in embryo-fetal studies in rats and rabbits administered oral miltefosine during organogenesis at doses that were respectively 0.06 and 0.2 times the maximum recommended human dose (MRHD), based on body surface area (BSA) comparison. Numerous visceral and skeletal fetal malformations were observed in a fertility study in female rats administered miltefosine prior to mating through day 7 of pregnancy at doses 0.3 times the MRHD. Do not administer IMPAVIDO to pregnant women.

Clinical Considerations

During pregnancy, visceral leishmaniasis may be life-threatening for the mother and may result in adverse fetal outcomes, including spontaneous abortion, congenital disease due to vertical transmission, small for gestational age newborn, and severe anemia. During pregnancy, cutaneous leishmaniasis may manifest with larger and atypical appearing lesions and may be associated with increased risk for adverse fetal outcomes, including preterm births and stillbirths.

Animal Data

Miltefosine administration in rat embryo-fetal toxicity studies during early embryonic development (Day 6 to Day 15 of gestation) caused embryo-fetal toxicity including death and teratogenicity at dosages of ≥ 1.2 mg/kg/day (0.06 times the MRHD based on BSA comparison). Teratogenic effects included undeveloped cerebrum, hemorrhagic fluid filling the lumina of the skull, cleft palate and generalized edema. Embryo-fetal toxicity was also observed in rabbits after oral administration of miltefosine during organogenesis (Day 6 to Day 18 of gestation) at doses ≥ 2.4 mg/kg/day (0.2 times the MRHD based on BSA comparison). In both rats and rabbits, there were no viable litters at miltefosine doses ≥ 6.0 mg/kg/day (0.3 or 0.6 times the MRHD based on BSA comparisons for rats and rabbits respectively).

In a separate female fertility study in rats, miltefosine doses ≥ 6.81 mg/kg/day (0.3 times the MRHD based on BSA comparison) administered for four weeks before mating and up to Day 7 of pregnancy produced numerous visceral (misshapen cerebral structures, dilated ventricles filled with brown masses, misshapen spinal cord, misshapen and malpositioned eyes, hypophysis, and absent inner ear) and skeletal (cleft palate, dumbbell-shaped ossification of thoracic vertebral centers, markedly enlarged skull bones, and markedly dilated suturae) fetal malformations. [see Contraindications (4.1), Nonclinical Toxicology (13.1)] .

8.3 Nursing Mothers

It is not known whether IMPAVIDO is present in human milk. Because many drugs are present in human milk and because of the potential for serious adverse reactions in nursing infants from IMPAVIDO, a decision should be made whether to discontinue nursing or discontinue the drug, taking into account the importance of the drug to the mother. Breastfeeding should be avoided for 5 months after IMPAVIDO therapy.

8.4 Pediatric Use

Safety and effectiveness in pediatric patients < 12 years have not been established. Juvenile rats were more sensitive to the miltefosine-induced effects, especially retinal and kidney effects, than adult rats [see Indications and Usage (1)] .

8.5 Geriatric Use

Clinical studies of IMPAVIDO did not include sufficient numbers of subjects 65 years of age and over to determine if they respond differently than younger subjects.

8.6 Renal Impairment

Patients with serum creatinine or BUN levels ≥1.5 times the upper limit of normal were excluded from the clinical studies. Miltefosine pharmacokinetics have not been studied in patients with renal impairment.

8.7 Hepatic Impairment

Patients with serum levels of ALT or AST ≥3 times the upper limit of normal and bilirubin levels ≥2 times the upper limit of normal were excluded from the clinical studies. Miltefosine pharmacokinetics have not been studied in patients with hepatic impairment.

8.8 Females and Males of Reproductive Potential

Contraception

IMPAVIDO may cause fetal harm when used during pregnancy. Advise females of reproductive potential to use effective contraception during IMPAVIDO therapy and for 5 months after therapy is completed [see Boxed Warning, Warnings and Precautions (5.1) and Use in Specific Populations (8.1)] .

Vomiting and/or diarrhea occurring during IMPAVIDO therapy may affect absorption of oral contraceptives and therefore may compromise their efficacy. Advise females who use oral contraceptives to use additional non-hormonal or alternative method(s) of effective contraception during IMPAVIDO therapy if vomiting and/or diarrhea occurs during therapy [see Warnings and Precautions (5.7)] .

Infertility

Females

Miltefosine caused impaired fertility in rats and caused reversible follicular atresia and diestrus in dogs at doses approximately 1.0 and 0.2 times respectively the MRHD [see Warnings and Precautions (5.2), Nonclinical Toxicology (13.1)] . The effects of IMPAVIDO on human female fertility have not been formally studied.

Males

Miltefosine caused reduced viable sperm counts and impaired fertility in rats at doses approximately 0.4 times the MRHD [see Warnings and Precautions (5.2), Nonclinical Toxicology (13.1)] . A higher dose in rats, approximately 1.0 times the MRHD, caused testicular atrophy and impaired fertility that did not fully reverse 10 weeks after drug administration ended. The effects of IMPAVIDO on human male fertility have not been adequately studied.

Advise women and men of the animal fertility findings, and that the potential for impaired fertility with IMPAVIDO therapy has not been adequately evaluated.

10 OVERDOSAGE

The common adverse effects of vomiting, diarrhea, and abdominal pain are likely in case of overdose. Institute adequate hydration to prevent the risk of impaired renal function, and replace electrolytes as necessary. Because miltefosine is only slightly excreted in the urine, forced diuresis will not increase miltefosine excretion. Gastrointestinal lavage is of unknown value. A specific antidote to treat miltefosine overdose is not known.

11 DESCRIPTION

IMPAVIDO capsules contain the active ingredient miltefosine, an antileishmanial agent. The chemical name of miltefosine is 2-[[(hexadecyloxy)hydroxyphosphenyl]oxy]-N,N,N-trimethylethylammonium inner salt. Miltefosine is a white powder that is freely soluble in water, 0.1 N HCl or NaOH, methanol, and ethanol. It has the empirical formula of C21H46NO4P with a molecular weight of 407.6 and the following structural formula:

The inactive ingredients are colloidal silicon dioxide, microcrystalline cellulose, lactose monohydrate, talc, and magnesium stearate. The capsule shell contains gelatin, titanium dioxide, ferric oxide, and purified water.

12 CLINICAL PHARMACOLOGY

12.1 Mechanism of Action

Miltefosine is an anti-leishmanial agent [see Clinical Pharmacology (12.4)] .

12.3 Pharmacokinetics

The pharmacokinetic parameters of miltefosine in patients with visceral and cutaneous leishmaniasis treated for 28 days with IMPAVIDO are listed in Table 5. Due to the long half-life of miltefosine (> 6 days), trough plasma concentrations did not appear to reach a steady state at the end of treatment (i.e., Day 28).

Table 5: Mean (%CV) Pharmacokinetic Parameters for Miltefosine Following Oral Capsule Administration to Adult Patients with Visceral and Cutaneous Leishmaniasis
 | Dose | Cmax (µg/mL) | Tmaxd (hr) | AUCtaue (µg∙hr/mL) | t1/2,αf (day) | t1/2,βg (day)
Visceral Leishmaniasis (on Day 23) | 50 mg BID (4 wks)a | 66.2 (28.5) | 7(2-12) | 636 (26.7) | 6.4 (31.1)
Visceral Leishmaniasis (on Day 23) | 50 mg BID (1 wk)/ 50 mg TID (3 wks)b | 75.9 (17.6) | 4 (2-8) | 486 (18.1) | 8.5 (28.9)
Cutaneous Leishmaniasisc (on Day 27) | 50 mg TID (4 wks) | 37.3 (22)f |  | 295 (22)f | 6.8 (5.8)g,h | 30.7 (18.3)g,h
a: Adolescent (≥12 years)/Adults, mean dose per kg was 3.1 mg/kg/day
b: Adolescent (≥12 years)/Adults, mean dose per kg was 3.6 mg/kg/day
c: Adults, mean dose per kg was 1.8 mg/kg/day
d: median (range)
e: AUC0-12h for BID, AUC0-8h for TID
f: t1/2,α = distribution phase half-life; t1/2,β = terminal elimination phase half-life
g: Estimates based on a population PK model
h: mean (% standard error)

Absorption

Absolute bioavailability of miltefosine has not been determined. In patients with visceral leishmaniasis, maximum miltefosine concentrations following oral administration of IMPAVIDO capsules were reached right before the next dose in many patients, indicating that the absorption of miltefosine may proceed throughout the dosing interval.

Distribution

The distribution of miltefosine has not been studied in humans. Human plasma protein binding of miltefosine, evaluated by an ultracentrifugation method, was 98% over the drug concentration range from 0.1 to 10 µg/mL. In rats, radioactivity of [^14C] miltefosine is widely distributed after both single and repeated oral administration with highest uptake of radioactivity in kidney, liver, and spleen. Placental transfer and excretion into milk have not been investigated.

Metabolism and Excretion

No in vitro oxidative metabolism by 15 different human cytochrome P450 enzymes (1A1, 1A2, 1B1, 2A6, 2B6, 2C8, 2C9, 2C18, 2C19, 2D6, 2E1, 3A4, 3A5, 3A7, and 4A1) was observed.

A slow metabolic breakdown could be shown in human hepatocytes, resulting in the release of choline by phospholipase D-like cleavage of the miltefosine molecule. The fatty alcohol-containing fragment of miltefosine can enter the metabolism of fatty acids after being oxidized to palmitic acid. This oxidation is blocked in patients with Sjögren-Larsson syndrome, which is caused by a genetic defect in fatty aldehyde dehydrogenase activity. IMPAVIDO is contraindicated in patients who have Sjögren-Larsson-Syndrome [see Contraindications (4.2)] .

There was little or no evidence of time or metabolism dependent inhibition of the cytochrome P450 enzymes examined at up to approximately 40 µg/mL miltefosine.

Oral administration of miltefosine did not markedly induce the content of hepatic CYP3A assayed by demethylation activity of erythromycin in rats.

In visceral leishmaniasis patients, <0.2% of the administered dose was excreted into the urine.

12.4 Microbiology

Mechanism of Action

The specific mode of action of miltefosine against Leishmania species is unknown. The mechanism of action of miltefosine is likely to involve interaction with lipids (phospholipids and sterols), including membrane lipids, inhibition of cytochrome c oxidase (mitochondrial function), and apoptosis-like cell death.

Activity In Vitro and In Vivo

Miltefosine has anti-leishmanial activity in vitro and in clinical infections [see Clinical Studies (14)] . Sensitivity of different Leishmania species as well as different strains of a Leishmania species to miltefosine may vary in different geographic regions.

Drug Resistance

In vitro studies show a potential for development of resistance to miltefosine. Some strains of L. braziliensis with intrinsic resistance to miltefosine have been identified . However, the clinical relevance of these observations is not known.

Drug resistance could be due to a decrease in miltefosine accumulation within Leishmania parasite which is thought to be due to either an increase in drug efflux, mediated by the overexpression of the ABC transporter P-glycoprotein and/or a decrease in drug uptake by the inactivation of the miltefosine transport machinery that consists of the miltefosine transporter and its beta subunit. Mutation in the transporter gene was reported in the isolates from a relapsed patient in one study. However, the clinical relevance of these findings is not known.

13 NONCLINICAL TOXICOLOGY

13.1 Carcinogenesis, Mutagenesis, Impairment of Fertility

Mutagenicity/Carcinogenicity: Miltefosine tested negative in the AMES-Salmonella test, DNA-amplification test, chromosomal aberration test in vitro, UDS-test in vivo/in vitro, and oral mouse micronucleus test in vivo. The V 79 mammalian cell HPRT gene mutation test showed an increase in mutant frequency without dose dependency. In view of all mutagenicity test results, the single positive finding in the V 79 HPRT test is considered to be not of toxicological relevance with respect to a mutagenic risk to humans.

Carcinogenicity studies were not performed. In a 52-week oral rat toxicity study, testicular Leydig cell adenoma was observed in 3 of 30 male rats with daily administration of 21.5 mg/kg/day miltefosine (1.0 times the MRHD based on BSA comparison). The carcinogenic potential of miltefosine in humans is unknown.

In a Segment I fertility study in male rats, testicular atrophy, reduced numbers of viable sperm, and impaired fertility were observed in rats following daily oral doses of ≥ 8.25 mg/kg (0.4 times the MRHD based on BSA comparison). These findings were reversible within a recovery period of 10 weeks except at the highest dose tested, 21.5 mg/kg/day (1.0 times the MRHD based on BSA comparison), where effects were not fully reversible.

In a female fertility study in rats, estrus cycle arrest in the metestrus or diestrus phases occurred with the high-dose of 21.5 mg/kg (1.0 times the MRHD based on BSA comparison). At doses of 6.81 and 21.5 mg/kg (0.3 and 1.0 times the MRHD respectively based on BSA comparison) increased numbers of embryonic and fetal resorptions and dead fetuses were observed. In a 52-week toxicology study in dogs, increased numbers of atretic follicles in the ovaries, and cycle arrest in the uterus, vagina, and mammary gland with morphology consistent with anestrus or diestrus was observed at doses ≥ 1 mg/kg/day (0.2 times the MRHD based on BSA comparison). The effects in dogs were fully reversible after a recovery period of 6 weeks.

13.2 Animal Toxicology and/or Pharmacology

Toxicological studies with miltefosine have been performed in mice, rats, dogs, and rabbits. Adverse reactions not observed in clinical studies but seen in animals at exposure levels similar to clinical exposure levels and with possible relevance to clinical use were as follows:

Acute and chronic toxicity: The oral administration of miltefosine in rats was associated with lesions affecting the eyes (retinal degeneration). Retinal degeneration was observed after 8-weeks treatment at doses of 10 mg/kg/day (0.5 times the MRHD based on BSA comparison). Juvenile rats were more sensitive to the miltefosine-induced effects, especially on eyes and kidneys, than adult rats with retinal degeneration occurring at doses ≥ 2.15 mg/kg/day (0.1 times the MRHD based on BSA comparison), and reversible damage to proximal tubule epithelium occurring at doses ≥ 4.64 mg/kg/day (0.2 times the MRHD based on BSA comparison).

14 CLINICAL STUDIES

14.1 Treatment of Visceral Leishmaniasis

One randomized, open-label, active-controlled study was conducted to evaluate the efficacy of IMPAVIDO in the treatment of visceral leishmaniasis in Bihar, India, an area where L. donovani is known epidemiologically to be the prevalent infecting species. Patients ≥ 12 years of age with clinical signs and symptoms compatible with visceral leishmaniasis (fever, splenomegaly, and cytopenia) confirmed by the presence of Leishmania amastigotes in aspirates of spleen or bone marrow were randomized to receive oral IMPAVIDO or intravenous amphotericin B deoxycholate in a 3:1 ratio. Patients weighing ≥ 25 kg received an IMPAVIDO 50 mg capsule with meals twice a day. Patients weighing < 25 kg received an IMPAVIDO 50 mg capsule with meals once a day in the morning. Weight ranged between 15 and 67 kg (mean weight 38.6 kg) and BMI ranged between 8.2 and 24 (mean 16.1). No patient weighed more than 70kg. Amphotericin B was administered intravenously over 6 continuous hours at 1 mg/kg every other day for 15 doses. Patients were hospitalized for the duration of therapy.

Exclusion criteria included platelet count <50 × 10^9/L, white cell count <1 × 10^9/L, hemoglobin <6 g/100 mL, AST or ALT ≥3 times upper limit of the normal range, bilirubin ≥2 times upper limit of the normal range, serum creatinine or BUN >1.5 times upper limit of the normal range, prothrombin time >5 seconds above control, and any non-compensated or uncontrolled condition including human immunodeficiency virus (HIV) infection. Women of reproductive potential were required to use effective contraception for the duration of therapy and for 2 months post therapy.

Final cure was defined as initial cure at end of therapy plus absence of signs and symptoms of visceral leishmaniasis at 6 months follow up. Initial cure at the end of therapy was evaluated by repeat spleen or bone marrow aspiration. Patients with initial parasitologic cure were followed for 6 months; patients without absence of clinical signs and symptoms of visceral leishmaniasis were to be evaluated with repeat spleen or bone marrow aspiration to determine final cure.

Two hundred and ninety nine (299) patients received IMPAVIDO and 99 patients received amphotericin B. Approximately, 70% of patients in each arm had previously failed treatment with pentavalent antimony. Initial cure was achieved in 98% of patients in each treatment arm. At 6 months after therapy, 88 (29.5%) IMPAVIDO recipients and 12 (12.1%) amphotericin B recipients continued to have signs and symptoms suggestive of visceral leishmaniasis. These signs or symptoms were attributed to alternative diagnosis in 73 patients. The remaining 27 patients, all in the IMPAVIDO arm, underwent evaluation with splenic or bone marrow aspiration, and 9 (3.0%) were positive for Leishmania amastigotes, indicating relapse. The final cure rates for IMPAVIDO and amphotericin B were 94% and 97%, respectively.

Table 6: Efficacy of IMPAVIDO in Visceral Leishmaniasis in Patients ≥12 years of Age in India
 | IMPAVIDO N = 299 | Amphotericin B Deoxycholate N = 99
End of therapy
Initial Cure | 293 (98%) | 97 (98%)
6 months after therapy
Final Cure [The 95% exact confidence interval for the difference (IV Amphotericin B – IMPAVIDO) in final cure is (-3.0%, 6.8%).] | 282 (94%) | 96 (97%)
Treatment Failure | 9 (3%) | 0 (0)
Not Assessable | 8 (3%) | 3 (3%)

14.2 Treatment of Cutaneous Leishmaniasis

A placebo controlled study was performed in Colombia where L. panamensis and L. braziliensis are epidemiologically known to be the prevalent infecting Leishmania species, and in Guatemala where L. braziliensis is epidemiologically known to be the prevalent infecting species. The study included male and female patients older than 12 years of age who had newly diagnosed or relapsing cutaneous leishmaniasis without mucosal involvement, parasitologically confirmed, presenting with at least one skin ulcer with minimum area of 50 mm^2. Exclusion criteria were AST or ALT ≥2 times upper limit of normal range, bilirubin ≥1.5 times upper limit of normal range, and serum creatinine or BUN >1.5 times upper limit of normal range. Women of reproductive potential were required to use effective contraception for the duration of therapy and for 2 months post therapy.

Patients were randomized to receive IMPAVIDO or placebo in a 2:1 allocation. Patients who weighed < 45 kg received IMPAVIDO 50 mg capsule twice a day, and patients who weighed ≥45 kg received IMPAVIDO 50 mg capsule three times a day. No patient weighed more than 84 kg. Definite cure was defined as apparent (complete epithelialization of all lesions) or partial cure (incomplete epithelialization, no enlargement by > 50% in lesions, no appearance of new lesions, and negative parasitology if done) at 2 weeks after end of therapy and complete epithelialization of all ulcers at 6 months after end of therapy. The definite cure rate for IMPAVIDO was statistically significantly higher than the cure rate for placebo.

Table 7: Efficacy of IMPAVIDO Compared to Placebo in the Treatment of Cutaneous Leishmaniasis in Colombia and Guatemala
 | IMPAVIDO | Placebo
Definite Cure [The difference (95% CI) between groups is 36.8% (20.1%, 53.4%) with P-value<0.0001.] | 59/89 (66%) | 13/44 (30%)
Colombia | 40/49 (82%) | 9/24 (38%)
Guatemala | 19/40 (48%) | 4/20 (20%)

An additional study of IMPAVIDO was conducted in Bahia and Manaus, two regions in Brazil where respectively L. braziliensis and L. guyanensis are epidemiologically the prevalent infecting pathogens. Adolescent/adult patients aged 12-65 years received IMPAVIDO orally for 28 days. IMPAVIDO target dose was 2.5 mg/kg/day: patients weighing 15-29 kg received 50 mg once daily, patients weighing 30-45 kg received 50 twice mg daily and patients weighing > 46 kg received 50 mg three times daily. The efficacy criteria were initial cure (complete re-epithelialization of the ulcer at 2 months after the end of therapy) followed by definite cure (complete re-epithelialization at 6 months after the end of therapy). Definite cure rate in patients aged ≥12 years was 27/40 (67.5%) for Manaus, Brazil and 34/40 (85%) for Bahia, Brazil.

14.3 Treatment of Mucosal Leishmaniasis

A single arm study was conducted to evaluate the efficacy of IMPAVIDO capsules for the treatment of mucosal leishmaniasis. The study was conducted in Bolivia where L. braziliensis is epidemiologically the prevalent species.

Seventy nine (79) patients ≥18 years of age with a cutaneous leishmaniasis scar plus parasites observed or cultured from lesion material or a positive skin test, andno clinically significant concomitant disease received miltefosine at a target dose of 2.5 mg/kg/day for 28 days.By 12 months after the end of therapy, 49 of the patients (62%) had complete resolution of edema, erythema, infiltration and erosion from the involved mucosal sites.

16 HOW SUPPLIED/STORAGE AND HANDLING

Each IMPAVIDO capsule contains 50 mg miltefosine in an opaque, red, hard gelatin capsule. IMPAVIDO capsules are supplied in a folded peel/push-through child-resistant blister card. Each blister card contains 14 capsules. Each carton contains two blister cards (NDC 69051-300-01).

Store at 20-25 °C (68-77 °F); excursions permitted to 15-30 °C (59-86 °F). [See USP Controlled Room Temperature]. Protect from moisture.

Dispense only in the original carton.

17 PATIENT COUNSELING INFORMATION

See the FDA-approved Medication Guide

17.1 Dosing Instructions

- IMPAVIDO is administered with food to ameliorate gastrointestinal side effects.
- Instruct the patient to swallow the capsule whole and not to chew it or break it apart. Instruct the patient to complete the full course of therapy.
- Inform the patient that abdominal pain, nausea, vomiting, and diarrhea are common side effects of therapy with IMPAVIDO and instruct the patient to inform their healthcare provider if these gastrointestinal side effects are severe or persistent. Instruct the patient to consume sufficient fluids to avoid dehydration and, consequently, the risk of kidney injury.

17.2 Females and Males of Reproductive Potential

- Advise women of reproductive potential to use effective contraception during IMPAVIDO therapy and for 5 months after therapy ends [see Boxed Warning and Use in Specific Populations (8.1, 8.8)] .
- Advise women who use oral contraceptives to use additional non-hormonal or alternative method(s) of effective contraception during IMPAVIDO therapy if vomiting and/or diarrhea occurs [see Warnings and Precautions (5.7) and Use in Specific Populations (8.8)] .
- Advise nursing mothers not to breastfeed during IMPAVIDO therapy and for 5 months after therapy is completed [see Use in Specific Populations (8.3)] .
- Advise women and men that IMPAVIDO caused infertility in male rats, impaired fertility in female rats, and caused atresia in ovarian follicles in female dogs. Advise patients that the potential of impaired fertility in humans has not been adequately evaluated [see Warnings and Precautions (5.2) and Use in Specific Populations (8.8)] .

Distributed by:
Profounda, Inc.
5790 Hoffner Avenue, Suite 507
Orlando, FL 32822
USA

PR033

Medication Guide

IMPAVIDO® (Im-PA-vee-do)
(miltefosine)
Capsules

Read this Medication Guide before you receive IMPAVIDO. This information does not take the place of talking to your healthcare provider about you medical condition or treatment.

What is the most important information I should know about IMPAVIDO?

IMPAVIDO may cause serious risks to pregnancy:

- Do not take IMPAVIDO if you are pregnant. If you take IMPAVIDO during pregnancy, your baby is at risk for death or serious birth defects.
- Women who can become pregnant should use effective birth control (contraception) during IMPAVIDO treatment and for 5 months after stopping IMPAVIDO treatment. Discuss with your healthcare provider which birth control method is right for you.
- If you become pregnant while taking IMPAVIDO, tell your healthcare provider right away. Talk to your healthcare provider about taking part in the IMPAVIDO Pregnancy Registry. This is a study to learn how IMPAVIDO affects pregnancy and babies. You can enroll in this registry by calling 1-866-588-5405.

What is IMPAVIDO?

IMPAVIDO is prescription medicine used to treat certain types of leishmaniasis:

- visceral leishmaniasis (affecting your internal organs)
- cutaneous leishmaniasis (affecting the skin)
- mucosal leishmaniasis (affecting the nose, mouth and throat)

It is not known if IMPAVIDO is safe and effective in children under 12 years of age.

Who should not take IMPAVIDO? Do not take IMPAVIDO if you:

- are pregnant
- have Sjögren-Larsson-Syndrome
- are allergic to miltefosine or any of the ingredients in IMPAVIDO. See the end of this leaflet for a list of the ingredients in IMPAVIDO.
- are a woman who can become pregnant and have not had a pregnancy test. Women who can get pregnant must have a urine or blood pregnancy test before taking IMPAVIDO.
- are a woman who can become pregnant and you are not willing to use effective birth control during IMPAVIDO treatment and for 5 months after treatment

Before you take IMPAVIDO, tell your healthcare provider about all of your medical conditions, including if you:

- have kidney or liver problems. Your healthcare provider should do blood tests to check your kidneys and liver before you start, during and after your treatment with IMPAVIDO.
- are pregnant or planning to become pregnant. IMPAVIDO may harm your unborn baby.
- are breastfeeding or plan to breastfeed. It is not known if IMPAVIDO passes into your breast milk. Talk to your healthcare provider about the best way to feed your baby if you take IMPAVIDO. You should avoid breastfeeding while you take IMPAVIDO and for 5 months after you stop taking IMPAVIDO.

Tell your healthcare provider about all the medicines you take, including prescription and over-the-counter medicines, vitamins, and herbal supplements.

How should I take IMPAVIDO?

- Take IMPAVIDO exactly as your healthcare provider tells you to.
- Complete your full 28 day IMPAVIDO treatment.
- Take IMPAVIDO capsules whole. Do not break, crush, dissolve, or chew IMPAVIDO before swallowing.
- Take IMPAVIDO with food to help reduce stomach problems.

What are the possible side effects of IMPAVIDO?

IMPAVIDO may cause serious side effects, including:

See “What is the most important information I should know about IMPAVIDO?”

- Fertility problems in male and female rats and abnormal menstrual cycle in female dogs. It is not known if IMPAVIDO causes fertility problems in men or women
- Testicular pain and absent or decreased ejaculation
- Kidney and liver problems
- Stomach problems. IMPAVIDO can cause vomiting, diarrhea, and dehydration. Call your healthcare provider right away if you have severe vomiting and diarrhea that does not go away. Drink a lot of water to help prevent dehydration while you are having vomiting and diarrhea.
- Decreased effectiveness of oral contraceptive pills. Vomiting and diarrhea may cause your birth control pills to be less effective at preventing pregnancy. Use an extra method of birth control, such as male condoms with spermicide, until you are no longer having vomiting and diarrhea.
- Decrease in platelets (which are blood cells that help blood clot).
- Serious Skin Problems. IMPAVIDO can cause a serious skin problem called Stevens-Johnson Syndrome. If you develop a skin rash with blisters while taking IMPAVIDO, stop taking IMPAVIDO right away and call your healthcare provider.

The most common side effects of IMPAVIDO include: nausea, vomiting and diarrhea. Other side effects include abdominal pain, decreased appetite, dizziness, headache, sleepiness, skin itching, and abnormalities in liver or kidney tests.

Tell your healthcare provider if you have any side effect that bothers you or that does not go away. These are not all the possible side effects of IMPAVIDO. For more information, ask your healthcare provider.

You may report side effects to FDA at 1-800-FDA-1088.

How should I store IMPAVIDO?

- Store IMPAVIDO at room temperature between 68°F to 77°F (20°C to 25°C).
- Protect IMPAVIDO from moisture.

Keep IMPAVIDO and all medicines out of the reach of children.

General information about the safe and effective use of IMPAVIDO.

Medicines are sometimes prescribed for purposes other than those listed in this Medication Guide. Do not use IMPAVIDO for a condition for which it was not prescribed. This Medication Guide summarizes the most important information about IMPAVIDO. If you would like more information, talk to your healthcare provider or pharmacist. You can ask your healthcare or pharmacist for information about IMPAVIDO that is written for health professionals. Do not give IMPAVIDO to other people, even if they have the same symptoms that you have. For more information, go to www.IMPAVIDO.com or www.dailymed.nlm.nih.gov, or call 1-866-588-5405.

What are the ingredients in IMPAVIDO?

Active ingredient: miltefosine

Inactive ingredients: colloidal silicon dioxide, microcrystalline cellulose, lactose monohydrate, talc, and magnesium stearate. The capsule shell contains gelatin, titanium dioxide, ferric oxide, and purified water.

Distributed by: Profounda, Inc.

This Medication Guide has been approved by the U.S. Food and Drug Administration.

Issued: Oct 2015

PR034

PRINCIPAL DISPLAY PANEL - CARTON

NDC 69051-300-01 28 Capsules

Impavido®
(miltefosine) capsules
50 mg per Capsule

Rx only PROFOUNDA

Contains 2 blister cards, 14 blisters per card, 1 capsule per blister.
Active ingredient: miltefosine
Inactive ingredients: colloidal silicon dioxide, lactose monohydrate,
magnesium stearate, microcrystalline cellulose, talc. The capsule shell
contains gelatin, titanium dioxide, ferric oxide and purified water.

Usual dosage: see enclosed package insert for complete
prescribing information.

Keep out of reach of children.

Store at 20-25 °C (68-77 °F); excursions permitted
to 15-30 °C (59-86 °F). [See USP Controlled Room Temperature].

Distributed by:
Profounda, Inc.
5790 Hoffner Avenue, Suite 507
Orlando, Florida 32822 USA